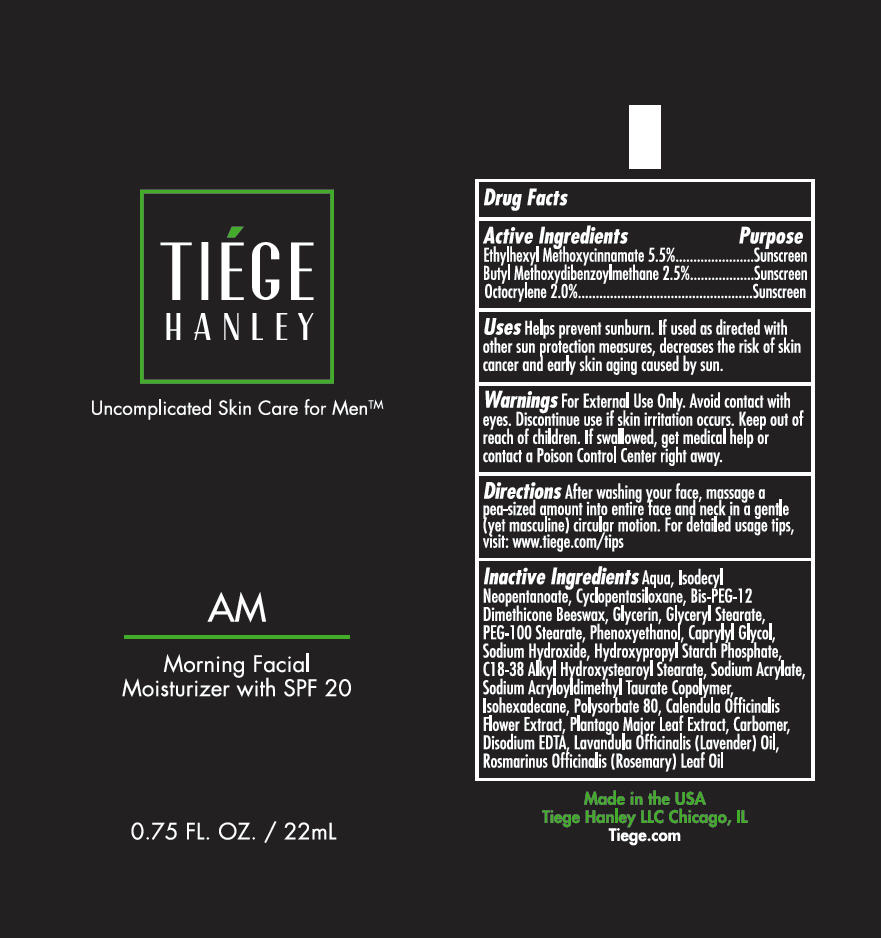 DRUG LABEL: Tiege Hanley AM Morning Facial Moisturizer with SPF20
NDC: 71714-020 | Form: LOTION
Manufacturer: Tiege hanley
Category: otc | Type: HUMAN OTC DRUG LABEL
Date: 20200109

ACTIVE INGREDIENTS: octinoxate 55 mg/1 mL; Avobenzone 25 mg/1 mL; octocrylene 20 mg/1 mL
INACTIVE INGREDIENTS: BIS-PEG-12 DIMETHICONE (70 MPA.S); CALENDULA OFFICINALIS FLOWER; TETRADECYLOCTADECYL STEARATE; Caprylyl Glycol; CARBOMER HOMOPOLYMER TYPE C (ALLYL PENTAERYTHRITOL CROSSLINKED); CYCLOMETHICONE 5; EDETATE DISODIUM ANHYDROUS; Glycerin; GLYCERYL MONOSTEARATE; HYDROXYPROPYL CORN STARCH (5% SUBSTITUTION BY WEIGHT); ISODECYL NEOPENTANOATE; ISOHEXADECANE; Lavender Oil; PEG-100 STEARATE; PHENOXYETHANOL; PLANTAGO MAJOR LEAF; POLYSORBATE 80; ROSEMARY OIL; SODIUM ACRYLATE/SODIUM ACRYLOYLDIMETHYLTAURATE COPOLYMER (4000000 MW); SODIUM HYDROXIDE; water

Tiége Hanley AM Morning Facial Moisturizer with SPF20

Drug Facts

ACTIVE INGREDIENT

Active Ingredients | Purpose
EthylMethoxycinnamate 5.5% | Sunscreen
Butyl Methoxydibenzoylmethane 2.5% | Sunscreen
Octocrylene 2.0% | Sunscreen

Uses

Helps prevent sunburn. If used as directed with Other sun protection measures, decreases the risk of skin cancer and early skin aging cause by sun.

Warnings

For External Use Only. Avoid contact with Eyes. Discontinue use if skin irritation occurs.

Keep out of reach of children. If swallowed, get medical help or contact a Poison Control Center right away.

Directions

After washing your face, massage a pea-sized amount into entire face and neck in a gentle (yet masculine) circular motion. For detailed usage tips, visit: www.tiege.com/tips

Inactive Ingredients

Aqua, Isocecyl Neopentanoate, Cyclopentasiloxane, Bis-PEG-12 Dimethicone Beeswax, Glycerin, Glyceryl Stearate, PEG-100 Stearate, Phenoxyethanol, Caprylyl Glycol, Sodium Hydroxide, HydroxypropylStarch Phosphate, C18-38 Alkyl Hydroxystearoyl Stearate, Sodium Acrylate, Sodium Acryloyldimethyl Taurate Copolymer, Isohexadecane, Polysorbate 80 , Calendula Officinalis Flower Extract, Plantago Major Leaf Extract, Carbomer, Disodium EDTA, Lavandula Officinalis (Lavender) Oil, Rosmarinus Officinalis (Rosemary) Leaf Oil

PRINCIPAL DISPLAY PANEL - 22 mL Tube Label

TIÉGE
HANLEY

Uncomplicated Skin Care for Men™

AM

Morning Facial
Moisturizer with SPF 20

0.75 FL. OZ. / 22mL